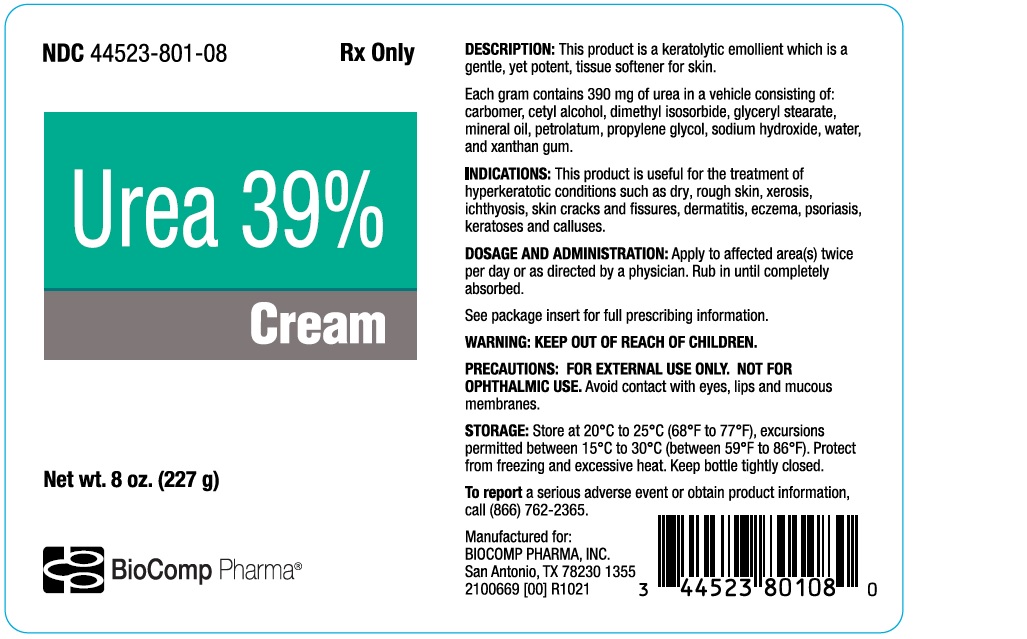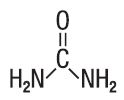 DRUG LABEL: Urea 39% Cream
NDC: 44523-801 | Form: CREAM
Manufacturer: BioComp Pharma, Inc.
Category: prescription | Type: HUMAN PRESCRIPTION DRUG LABEL
Date: 20260113

ACTIVE INGREDIENTS: UREA 390 mg/1 g
INACTIVE INGREDIENTS: MINERAL OIL; PETROLATUM; PROPYLENE GLYCOL; WATER; GLYCERYL MONOSTEARATE; XANTHAN GUM; DIMETHYL ISOSORBIDE; CARBOMER INTERPOLYMER TYPE A (55000 CPS); CETYL ALCOHOL; SODIUM HYDROXIDE

UREA CREAM 39%

GENERAL:

This product is to be used as directed by a physician and should not be used to treat any condition other than that for which it was prescribed. If redness or irritation occurs, discontinue use and consult a physician.

DESCRIPTION

This product is a keratolytic emollient which is a gentle, yet potent, tissue softener for skin.

Each gram contains 390 mg of urea in a vehicle consisting of: carbomer, cetyl alcohol, dimethyl isosorbide, glyceryl stearate, mineral oil, petrolatum, propylene glycol, sodium hydroxide, water, and xanthan gum.

Urea is a diamide of carbonic acid with the following chemical structure:

CLINICAL PHARMACOLOGY

Urea gently dissolves the intercellular matrix which results in loosening the horny layer of skin and shedding scaly skin at regular intervals, thereby softening hyperkeratotic areas of the skin.

PHARMACOKINETICS

The mechanism of action of topically applied urea is not yet known.

INDICATIONS:

This product is useful for the treatment of hyperkeratotic conditions such as dry, rough skin, xerosis, ichthyosis, skin cracks and fissures, dermatitis, eczema, psoriasis, keratoses and calluses.

CONTRAINDICATIONS

This product is contraindicated in persons with known or suspected hypersensitivity to any of the ingredients of the product.

KEEP OUT OF REACH OF CHILDREN.

PRECAUTIONS

FOR EXTERNAL USE ONLY. NOT FOR OPHTHALMIC USE.

PATIENT COUNSELING INFORMATION

Patients should discontinue the use of this product if the condition becomes worse or if a rash develops in the area being treated or
elsewhere. Avoid contact with eyes, lips and mucous membranes.

CARCINOGENESIS AND MUTAGENESIS AND IMPAIRMENT OF FERTILITY

Long-term animal studies for carcinogenic potential have not been performed on this product to date. Studies on reproduction and fertility also have not been performed.

PREGNANCY

Category C.Animal reproduction studies have not been conducted with this product. It is also not known whether this product can affect reproduction capacity or cause fetal harm when administered to a pregnant woman. This product should be used by a pregnant woman only if clearly needed or when potential benefits outweigh potential hazards to the fetus.

NURSING MOTHERS

It is not known whether this drug is excreted in human milk. Because many drugs are excreted in human milk, caution should be exercised when this product is administered to a nursing woman.

ADVERSE REACTIONS

Transient stinging, burning, itching or irritation may occur and normally disappear upon discontinuing the use of this product.

DOSAGE AND ADMINISTRATION

Apply to affected area(s) twice per day or as directed by a physician. Rub in until completely absorbed.

STORAGE AND HANDLING

Store at 20°C to 25°C (68°F to 77°F), excursions permitted between 15°C to 30°C (between 59°F to 86°F). Brief exposure to
temperatures up to 40°C (104°F) may be tolerated provided the mean kinetic temperature does not exceed 25°C (77°F); however, such exposure should be minimized.

NOTICE:

Protect from freezing and excessive heat. Keep bottle tightly closed.

HOW SUPPLIED

8 oz. (227 g) bottles, NDC 44523-801-08

To reporta serious adverse event or obtain product information, call (866) 762-2365.

Manufactured for:
BIOCOMP PHARMA, INC.
San Antonio, TX 78230 1355

2100669 [00] R1021